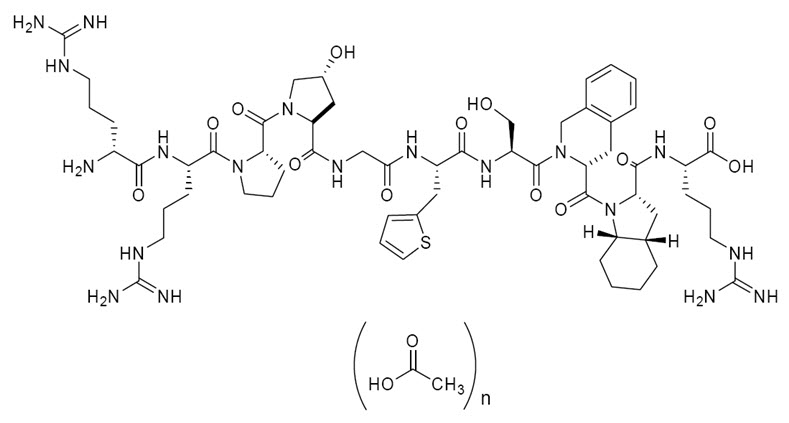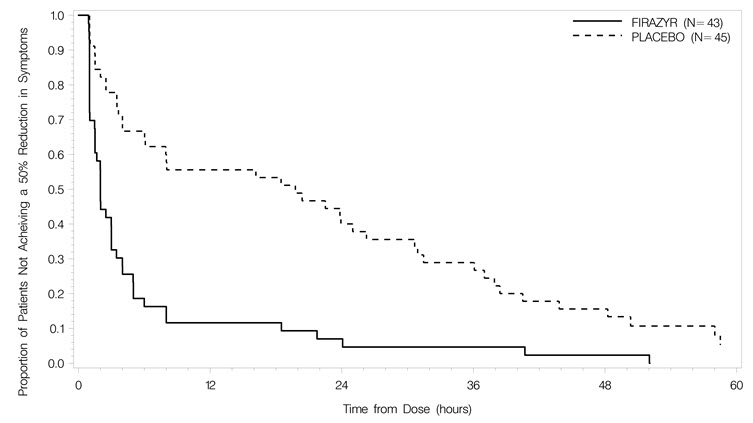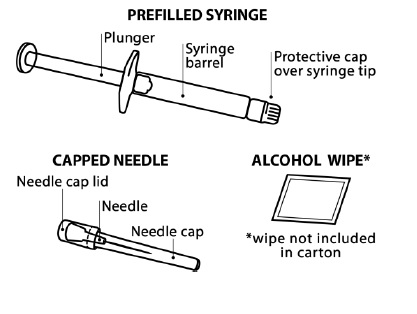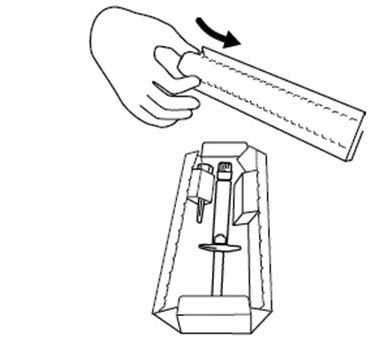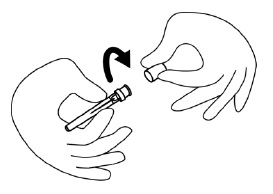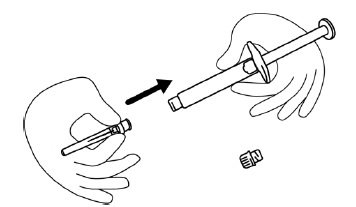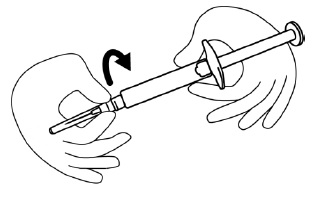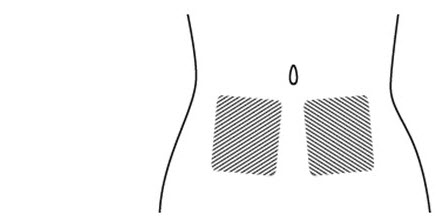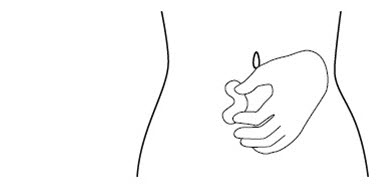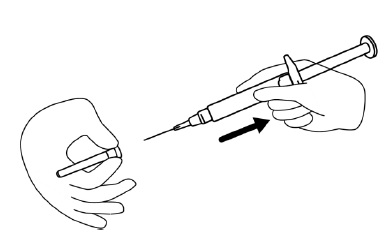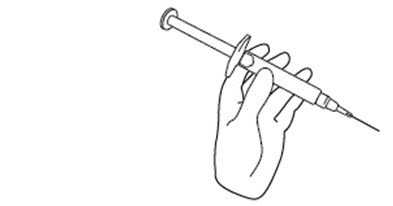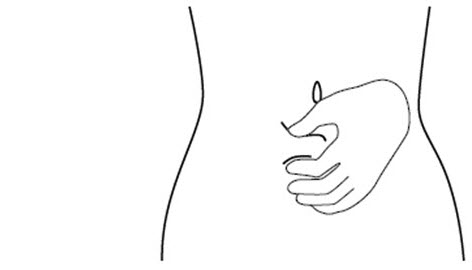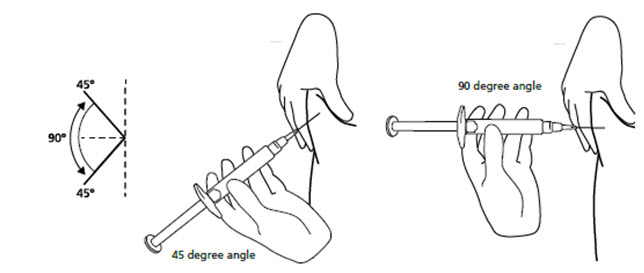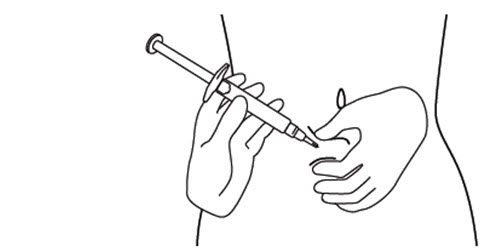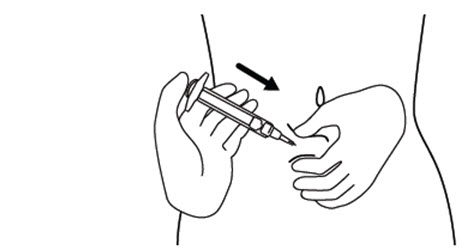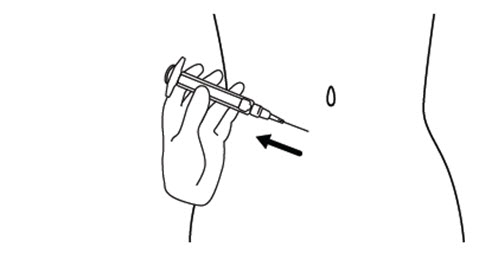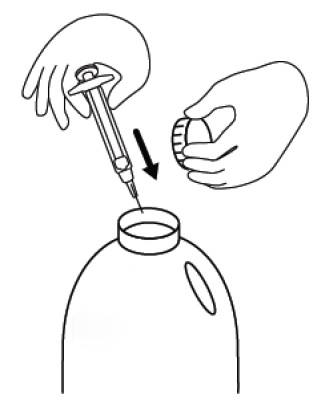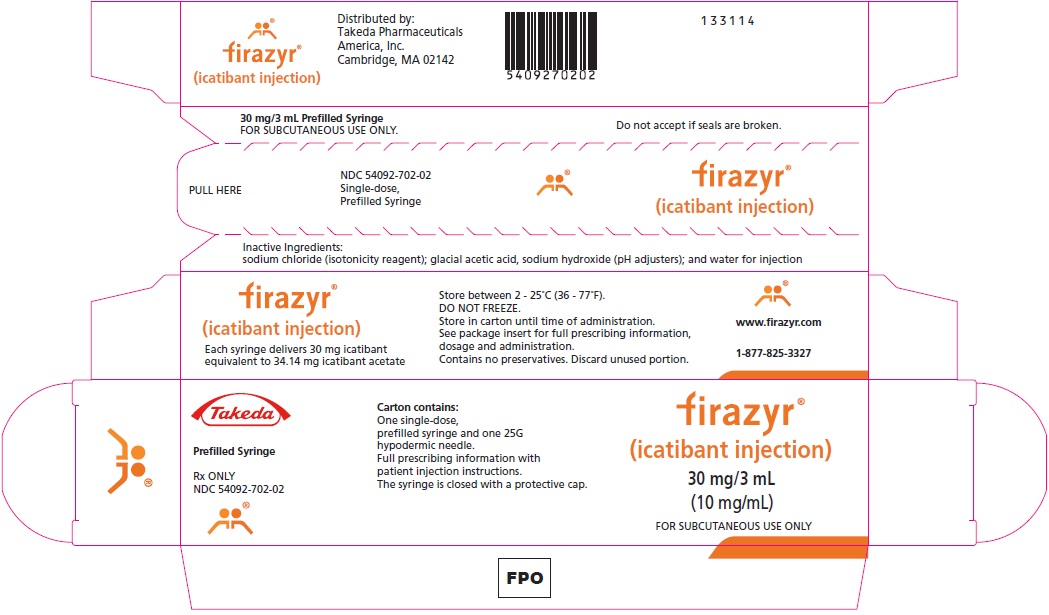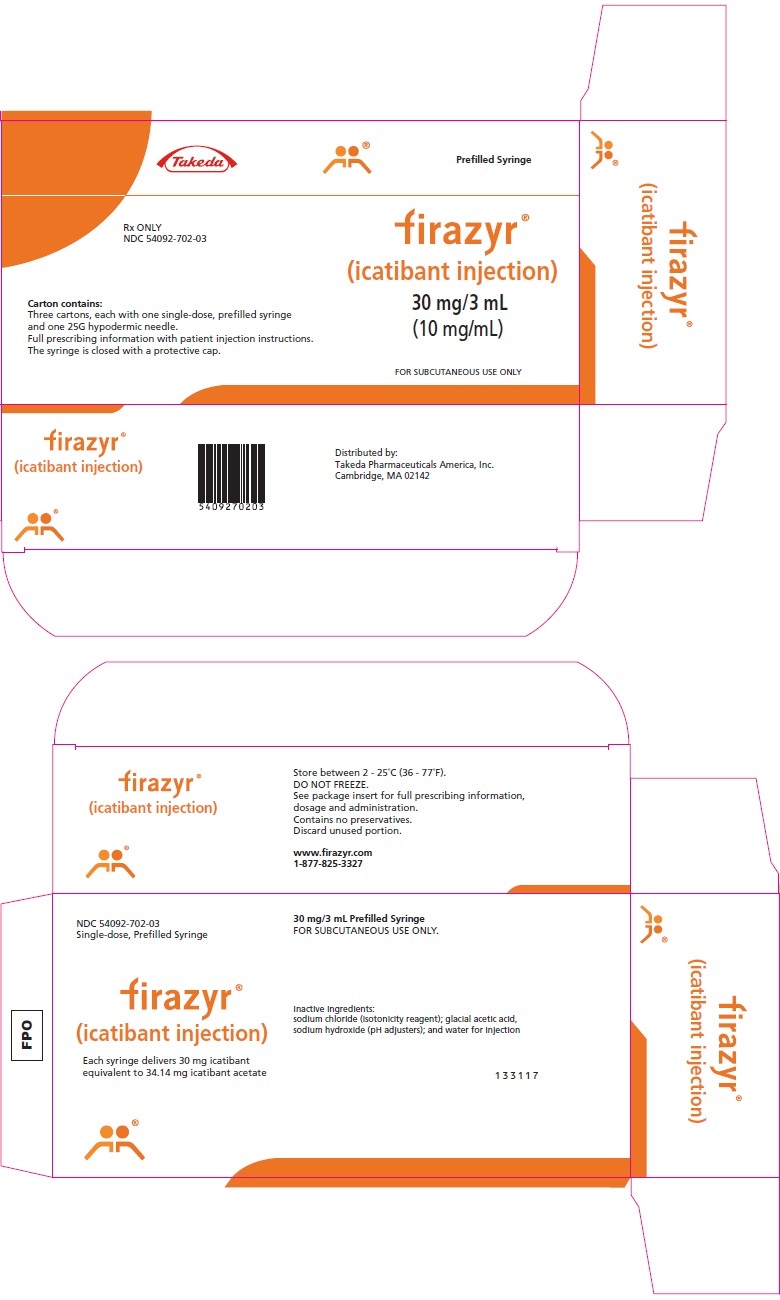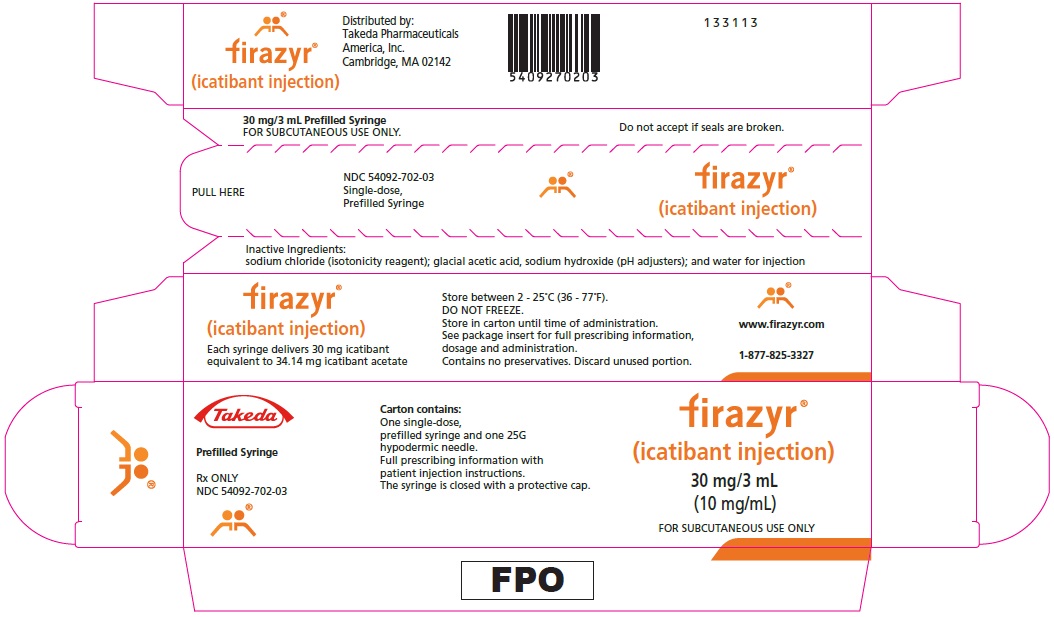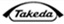 DRUG LABEL: Firazyr
NDC: 54092-702 | Form: INJECTION, SOLUTION
Manufacturer: Takeda Pharmaceuticals America, Inc.
Category: prescription | Type: HUMAN PRESCRIPTION DRUG LABEL
Date: 20250707

ACTIVE INGREDIENTS: icatibant acetate 30.0 mg/3 mL
INACTIVE INGREDIENTS: sodium hydroxide 1.92 mg/3 mL; acetic acid 3.96 mg/3 mL; sodium chloride 22.35 mg/3 mL; water

HIGHLIGHTS OF PRESCRIBING INFORMATION

These highlights do not include all the information needed to use FIRAZYR® (icatibant) safely and effectively. See full prescribing information for FIRAZYR.
FIRAZYR (icatibant) Injection, for subcutaneous use
Initial U.S. Approval: 2011

1 INDICATIONS AND USAGE

FIRAZYR is a bradykinin B2 receptor antagonist indicated for treatment of acute attacks of hereditary angioedema (HAE) in adults 18 years of age and older. (1)

2 DOSAGE AND ADMINISTRATION

- 30 mg injected subcutaneously in the abdominal area. (2.1)
- If response is inadequate or symptoms recur, additional injections of 30 mg may be administered at intervals of at least 6 hours. (2.1)
- Do not administer more than 3 injections in 24 hours. (2.1)
- Patients may self-administer upon recognition of an HAE attack. (2.2)

3 DOSAGE FORMS AND STRENGTHS

Injection: 10 mg per mL (3)

4 CONTRAINDICATIONS

None (4)

5 WARNINGS AND PRECAUTIONS

Laryngeal attacks: Following treatment of laryngeal attacks with FIRAZYR, advise patients to seek immediate medical attention. (5.1)

6 ADVERSE REACTIONS

The most commonly reported adverse reactions were injection site reactions, which occurred in almost all patients (97%) in clinical trials. Other common adverse reactions occurring in greater than 1% of patients included pyrexia, transaminase increase, dizziness, and rash. (6.1)

To report SUSPECTED ADVERSE REACTIONS, contact Takeda Pharmaceuticals America, Inc. at 1-877-TAKEDA-7 (1-877-825-3327) or FDA at 1-800-FDA-1088 or www.fda.gov/medwatch.

8 USE IN SPECIFIC POPULATIONS

Elderly patients demonstrate increased systemic exposure to icatibant. Differences in efficacy and safety between elderly and younger patients have not been identified. (8.5)

FULL PRESCRIBING INFORMATION

1 INDICATIONS AND USAGE

FIRAZYR® (icatibant) is indicated for the treatment of acute attacks of hereditary angioedema (HAE) in adults 18 years of age and older.

2 DOSAGE AND ADMINISTRATION

2.1 Recommended Dosing

The recommended dose of FIRAZYR is 30 mg administered by subcutaneous (SC) injection in the abdominal area. Additional doses may be administered at intervals of at least 6 hours if response is inadequate or if symptoms recur. No more than 3 doses may be administered in any 24 hour period.

2.2 Administration Instructions

FIRAZYR should be inspected visually for particulate matter and discoloration prior to administration. The drug solution should be clear and colorless. Do not administer if the product contains particulates or is discolored.

Attach the provided 25 gauge needle to the syringe hub and screw on securely. Do not use a different needle. Disinfect the injection site and administer FIRAZYR by subcutaneous injection over at least 30 seconds.

Patients may self-administer FIRAZYR upon recognition of symptoms of an HAE attack after training under the guidance of a healthcare professional [see Patient Counseling Information (17)].

3 DOSAGE FORMS AND STRENGTHS

FIRAZYR injection is supplied in a prefilled syringe delivering 30 mg icatibant. Each syringe delivers 3 mL solution with a concentration of 10 mg per mL.

4 CONTRAINDICATIONS

None.

5 WARNINGS AND PRECAUTIONS

5.1 Laryngeal Attacks

Given the potential for airway obstruction during acute laryngeal HAE attacks, patients should be advised to seek medical attention in an appropriate healthcare facility immediately in addition to treatment with FIRAZYR.

6 ADVERSE REACTIONS

6.1 Clinical Trials Experience

The safety of icatibant was evaluated in three controlled trials that included 223 patients who received FIRAZYR 30 mg (n=113), placebo (n=75), or comparator (n=38). The mean age at study entry was 38 years (range 18 to 83 years), 64% were female, and 95% were white. The data described below represent adverse reactions observed from the two placebo-controlled trials, consisting of 77 patients who received FIRAZYR at a dose of 30 mg SC, and 75 who received placebo.

The most frequently reported adverse reactions (occurring in greater than 1% of patients and at a higher rate with FIRAZYR versus placebo) are shown in Table 1.

Because clinical trials are conducted under widely varying conditions, adverse reaction rates observed in the clinical trials of a drug cannot be directly compared to rates in the clinical trials of another drug and may not reflect the rates observed in practice.

Table 1 Adverse reactions observed in >1% of patients with acute attacks of HAE and at a higher rate with FIRAZYR versus placebo in the placebo-controlled trials [Events occurring within 14 days of study drug administration]
 | FIRAZYR (N =77) | Placebo (N = 75)
System Organ Class Preferred Term | Subjects (%) | Subjects (%)
General disorders and administration site conditions
Injection site reaction [Injection site bruising, Injection site hematoma, Injection site burning, Injection site erythema, Injection site hypoesthesia, Injection site irritation, Injection site numbness, Injection site edema, Injection site pain, Injection site pressure sensation, Injection site pruritus, Injection site swelling, Injection site urticaria, and Injection site warmth] | 75 (97) | 25 (33)
Pyrexia | 3 (4) | 0
Investigations
Transaminase increased | 3 (4) | 0
Nervous system disorders
Dizziness | 2 (3) | 1 (1)

The third trial was active-controlled and was comprised of 35 patients who received FIRAZYR 30 mg and 38 patients who received the comparator. Adverse reactions for FIRAZYR were similar in nature and frequency to those reported in Table 1.

In all three controlled trials, patients were eligible for treatment of subsequent attacks in an open-label extension. Patients were treated with FIRAZYR 30 mg and could receive up to 3 doses of FIRAZYR 30 mg administered at least 6 hours apart for each attack. A total of 225 patients were treated with 1,076 doses of 30 mg FIRAZYR for 987 attacks of acute HAE. Adverse reactions similar in nature and frequency were observed to those seen in the controlled phase of the trials. Other adverse reactions reported included rash, nausea, and headache in patients exposed to FIRAZYR.

The safety of self-administration was evaluated in a separate, open-label trial in 56 patients with HAE. In this trial, the safety profile of FIRAZYR in patients who self-administered FIRAZYR was similar in nature and frequency to that of patients whose therapy was administered by healthcare professionals.

6.2 Immunogenicity

Across repeated treatment in the controlled trials, 4 patients tested positive for anti-icatibant antibodies. Three of these patients had subsequent tests which were negative. No hypersensitivity or anaphylactic reactions were reported with FIRAZYR. No association between anti-icatibant antibodies and efficacy was observed.

6.3 Postmarketing Experience

The following adverse reactions have been identified during post approval use of FIRAZYR: urticaria. Because these events are reported voluntarily from a population of uncertain size, it is not always possible to reliably estimate their frequency or establish a causal relationship to drug exposure.

7 DRUG INTERACTIONS

7.1 ACE Inhibitors

FIRAZYR is a bradykinin B2 receptor antagonist and thereby has the potential to have a pharmacodynamic interaction with ACE inhibitors where FIRAZYR may attenuate the antihypertensive effect of ACE inhibitors. Clinical trials to date have excluded subjects taking ACE inhibitors.

8 USE IN SPECIFIC POPULATIONS

8.1 Pregnancy

Risk Summary

Available data from published literature and the pharmacovigilance database with Firazyr (icatibant) use in pregnant women have not identified a drug-associated risk of major birth defects, miscarriage or adverse maternal or fetal outcomes. In animal reproduction studies, icatibant, administered by the subcutaneous route during the period of organogenesis, did not cause structural abnormalities in rats or rabbits; however, premature birth and abortion were observed in rabbits at doses approximately 0.025 times the maximum recommended human dose (MRHD) and higher. Decreased embryofetal survival was observed in rabbits at a subcutaneous dose that was 13 times the MRHD. In a pre- and post-natal development study in rats, delayed parturition was observed at subcutaneous doses 0.5 times the MRHD and higher, which resulted in deaths of dams at doses 2 times the MRHD and higher. Fetal death and early pup deaths were observed with doses 2 times the MRHD (see Data).

The estimated background risk of major birth defects and miscarriage for the indicated population is unknown. All pregnancies have a background risk of birth defect, loss, or other adverse outcomes. In the U.S. general population, the estimated background risk of major birth defects and miscarriage in clinically recognized pregnancies is 2% to 4% and 15% to 20%, respectively.

Data

Animal Data

In an embryo-fetal development study with rats that received icatibant from gestation days 7 to 18, there was no evidence of any treatment-related structural abnormalities or effects on embryo-fetal survival with maternal doses up to 2.7 times the MRHD (on a mg/m^2 basis with maternal subcutaneous doses up to 25 mg/kg/day). In a fertility and early embryonic development study with rats, icatibant increased pre-implantation loss at a dose that was 7 times the MRHD (on an AUC basis at a maternal dose of 10 mg/kg/day).

In an embryo-fetal development study with rabbits that received icatibant from gestation days 7 to 18, premature birth and abortion rates increased at doses approximately 0.025 times the MRHD and higher (on a mg/m^2 basis at maternal subcutaneous doses of 0.1 mg/kg and higher). Icatibant treatment resulted in dose-related decreases of total implantations and total number of live fetuses as well as dose-related increases of percent pre-implantation loss at a dose that was 13 times the MRHD (on an AUC basis with a maternal subcutaneous dose of 10 mg/kg/day). There was no evidence of any treatment-related structural abnormalities with maternal doses up to 13 times the MRHD (on an AUC basis with maternal subcutaneous doses up to 10 mg/kg/day).

In a pre- and post-natal development study in the rat, dams received icatibant by the subcutaneous route at doses of 1, 3, and 10 mg/kg/day from gestation day 6 to post-partum (PPD) day 20. Delayed parturition was observed at doses 0.5 times the MRHD and higher (on an AUC basis with maternal subcutaneous doses of 1 mg/kg/day and higher), which resulted in deaths of dams at doses 2 times the MRHD and higher (on an AUC basis with maternal subcutaneous doses of 3 mg/kg/day and higher). Fetal death and increased pup deaths through PPD 4 were observed with doses 2 times the MRHD (on an AUC with a maternal subcutaneous dose of 3 mg/kg/day and higher). Impairment of pup righting reflex and decreased pup hair growth were also observed at 7 times the MRHD (on an AUC basis with a maternal dose of 10 mg/kg). Icatibant and the M2 metabolite were found in maternal milk following subcutaneous administration of icatibant. The no effect dose for F1 pups was identified at a dose 0.5 times the MRHD (on an AUC basis with a maternal subcutaneous dose of 1 mg/kg/day). A no effect dose was not identified for F0 maternal toxicity.

8.2 Lactation

Risk Summary

There are no data on the presence of icatibant in human milk, the effects on the breastfed infant, or the effects on milk production. Icatibant and the M2 metabolite were found in rat milk following subcutaneous administration of icatibant (see Data). When a drug is present in animal milk, it is likely that the drug will be present in human milk. However, systemic absorption of icatibant in infants is not expected after oral exposure through breast milk. The developmental and health benefits of breastfeeding should be considered along with the mother's clinical need for FIRAZYR and any potential adverse effects on the breastfed child from FIRAZYR or from the underlying maternal condition.

Data

Animal Data

Icatibant is excreted into the milk of lactating rats at concentrations that sometimes slightly exceeded those measured in the maternal plasma.

8.4 Pediatric Use

Safety and effectiveness in pediatric patients below the age of 18 years have not been established.

Juvenile Toxicity Data

Subcutaneous daily administration of icatibant to young rats during the juvenile period of development (postnatal days 22-70) delayed the sexual maturation of male reproductive tissues (atrophy of testes and epididymides) at exposures approximating one-third or greater the MRHD on a mg/m^2 basis. Impaired fertility and reproductive performance were also observed in male rats at the end of the postnatal treatment period at exposures approximating the MRHD or greater on a mg/m^2 basis. No effects were observed in females at exposures approximating 3-fold the MRHD on a mg/m^2 basis. The observed tissue findings in males were consistent with those seen in sexually mature rats and dogs and are attributed to antagonism of the bradykinin B2 receptor and subsequent effects on gonadotropins. The observed effects may be a consequence of daily icatibant administration. Toxicity to the testis did not occur in dogs treated twice a week for 9 months [see Carcinogenesis, Mutagenesis, Impairment of Fertility (13.1)].

8.5 Geriatric Use

Clinical studies of FIRAZYR did not include sufficient numbers of subjects aged 65 and over to determine whether they respond differently from younger subjects. Elderly patients are likely to have increased systemic exposure to FIRAZYR compared to younger (18-45 years) patients [see Clinical Pharmacology (12.3)]. Since other reported clinical experience has not identified differences in efficacy and safety between elderly and younger patients, no dose adjustment is recommended.

8.6 Hepatic Impairment

FIRAZYR was studied in patients with mild to moderate (Child Pugh scores of 5 to 8) hepatic impairment. No change in systemic exposure is noted in these patient populations. No dose adjustment is required in patients with hepatic impairment [see Clinical Pharmacology (12.3)].

8.7 Renal Impairment

Although a formal renal impairment study has not been conducted, 10 of 37 patients treated with FIRAZYR had hepatorenal syndrome with glomerular filtration rate (GFR) below 60 mL/min. FIRAZYR is cleared non-renally and hence it is not expected to show any change in systemic exposure in patients with impaired renal function. No dose adjustment is required in patients with renal impairment [see Clinical Pharmacology (12.3)].

10 OVERDOSAGE

In a clinical study evaluating a 90 mg dose (30 mg in each of 3 subcutaneous sites), the adverse event profile was similar to that seen with 30 mg administered in a single subcutaneous site.

In another clinical study, a dose of 3.2 mg/kg administered intravenously (approximately 8 times the therapeutic dose for HAE) caused erythema, itching and hypotension in healthy subjects. No therapeutic intervention was necessary.

11 DESCRIPTION

FIRAZYR (icatibant) is a synthetic decapeptide with five non-proteinogenic amino acids. The chemical structure of icatibant acetate is presented in Figure 1.

Figure 1 Chemical Structure

Chemical name: D-Arginyl-L-arginyl-L-prolyl-L[(4R)-4-hydroxyprolyl]-glycyl-L[3-(2-thienyl)alanyl]-L-seryl-D-(1,2,3,4-tetrahydroisoquinolin-3-ylcarbonyl)-L[(3aS,7aS)-octahydroindol-2-ylcarbonyl]-L-arginine, acetate salt

FIRAZYR is provided as a sterile, isotonic, and buffered solution of icatibant acetate in a single-dose, prefilled syringe for subcutaneous administration. Each mL of the solution contains 10 mg of icatibant (free base) which is equivalent to 11.38 mg of icatibant acetate. Each prefilled syringe delivers 3 mL of solution equivalent to a 30 mg icatibant dose. The solution is clear and colorless.

The solution also contains sodium chloride (isotonicity reagent), glacial acetic acid (pH adjuster), sodium hydroxide (pH adjuster) and water for injection with a pH of approximately 5.5. The solution does not contain preservatives.

Pharmacological class: Icatibant is a bradykinin B2 receptor antagonist.

12 CLINICAL PHARMACOLOGY

12.1 Mechanism of Action

Icatibant is a competitive antagonist selective for the bradykinin B2 receptor, with an affinity similar to bradykinin. Hereditary angioedema is caused by an absence or dysfunction of C1-esterase-inhibitor, a key regulator of the Factor XII/kallikrein proteolytic cascade that leads to bradykinin production. Bradykinin is a vasodilator which is thought to be responsible for the characteristic HAE symptoms of localized swelling, inflammation, and pain. Icatibant inhibits bradykinin from binding the B2 receptor and thereby treats the clinical symptoms of an acute, episodic attack of HAE.

12.2 Pharmacodynamics

Following bradykinin challenge, intravenous administration of FIRAZYR caused dose and time-dependent inhibition of development of bradykinin-induced hypotension, vasodilation, and reflex tachycardia in healthy young subjects. FIRAZYR intravenous doses of 0.4 and 0.8 mg/kg infused over 4 hours inhibited response to bradykinin challenge for 6 to 8 hours following completion of the infusion. Based on exposure-response analysis, a subcutaneous dose of 30 mg FIRAZYR is predicted to be effective against bradykinin challenge for at least 6 hours. The clinical significance of these findings is unknown.

The effect of FIRAZYR 30 and 90 mg following a single subcutaneous injection on QTc interval was evaluated in a randomized, placebo-, and active-controlled (moxifloxacin 400 mg) four-period crossover thorough QT study in 72 healthy subjects. In a study with demonstrated ability to detect small effects, the upper bound of the one-sided 95% confidence interval for the largest placebo adjusted, baseline-corrected QTc based on individual correction method (QTcI) was below 10 ms, the threshold for regulatory concern. The dose of 90 mg is adequate to represent the high exposure clinical scenario.

12.3 Pharmacokinetics

The pharmacokinetics of FIRAZYR has been characterized in studies using both intravenous and subcutaneous administration to healthy subjects and patients. The pharmacokinetic profile of FIRAZYR in patients with HAE is similar to that in healthy subjects.

The absolute bioavailability of FIRAZYR following a 30 mg subcutaneous dose is approximately 97%. Following subcutaneous administration of a single 30 mg dose of FIRAZYR to healthy subjects (N=96), a mean (± standard deviation) maximum plasma concentration (Cmax) of 974 ± 280 ng/mL was observed after approximately 0.75 hours. The mean area under the concentration-time curve (AUC0-∞) after a single 30 mg dose was 2165 ± 568 ng∙hr/mL, with no evidence of accumulation of icatibant following three 30 mg doses administered 6 hours apart. Following subcutaneous administration, plasma clearance was 245 ± 58 mL/min with a mean elimination half-life of 1.4 ± 0.4 hours and volume of distribution at steady state (Vss) of 29.0 ± 8.7 L.

Icatibant is extensively metabolized by proteolytic enzymes to inactive metabolites that are primarily excreted in the urine, with less than 10% of the dose eliminated as unchanged drug. Icatibant is not degraded by oxidative metabolic pathways, is not an inhibitor of major cytochrome P450 (CYP) isoenzymes (CYP 1A2, 2A6, 2B6, 2C8, 2C9, 2C19, 2D6, 2E1, and 3A4) and is not an inducer of CYP 1A2 and 3A4.

Special populations

Hepatic Impairment

The pharmacokinetic parameters of FIRAZYR were found to be generally comparable between healthy subjects (n=8) and mild to moderate (Child Pugh scores of 5 to 8) hepatic impaired patients (n=8) following a dose of 0.15 mg/kg/day as continuous intravenous infusion over 3 days. In a separate study, FIRAZYR clearance in subjects with a wide range of hepatic impairment (Child-Pugh scores of 7 to 15) was similar to that in healthy subjects. No dose adjustment is necessary for patients with impairment of hepatic function [see Use in Specific Populations (8.6)].

Renal Impairment

Since renal clearance of icatibant is a minor eliminating pathway, renal impairment is not expected to affect the pharmacokinetics of FIRAZYR and hence a formal renal impairment study was not conducted for FIRAZYR. In 10 patients with hepatorenal syndrome (GFR 30-60 mL/min), clearance of FIRAZYR was not dependent on renal function and therefore, did not show any observable differences in the plasma levels of icatibant or its metabolites compared to subjects with normal renal function. No dose adjustment is necessary for patients with impairment of renal function [see Use in Specific Populations (8.7)].

Age and Gender

Three 30 mg subcutaneous doses of FIRAZYR administered every 6 hours were studied in young (18 to 45 years of age) and elderly (over 65 years of age) healthy male and female subjects. Following single-dose administration of 30 mg subcutaneous FIRAZYR, elderly males and females showed approximately 2-fold higher AUC compared to young males and females, respectively. However, only minor differences (~12-14%) between Cmax of gender–matched elderly and young subjects were observed. Older subjects tend to exhibit lower clearance compared to younger subjects and therefore higher systemic exposure. Gender effect on FIRAZYR pharmacokinetics was also observed in addition to age effect. Clearance of FIRAZYR is significantly correlated with bodyweight with lower clearance values noted for lower bodyweights. Hence, females with typically lower body weights compared to males exhibit lower clearance values, resulting in approximately 2-fold higher systemic exposure (both AUC and Cmax) compared to males. Differences in efficacy and safety between elderly and younger patients and male and female patients have not been identified. Dose adjustment based on age and gender is not warranted.

Drug Interactions

Formal drug-drug interaction studies were not conducted with FIRAZYR. Icatibant metabolism is not mediated by CYP450 enzymes. In vitro study did not show any significant inhibition and/or induction of drug metabolizing CYP450 enzymes; therefore, metabolic drug interactions between FIRAZYR and CYP450 substrates, inhibitors and inducers are not expected.

13 NONCLINICAL TOXICOLOGY

13.1 Carcinogenesis, Mutagenesis, Impairment of Fertility

Two-year studies were conducted in CD1 mice and Wistar rats to assess the carcinogenic potential of FIRAZYR. No evidence of tumorigenicity was observed in mice and rats at icatibant subcutaneous doses up to 15 mg/kg/day (twice per week) and 6 mg/kg/day (daily), respectively (approximately 10-fold and 6-fold greater than the MRHD on an AUC basis, respectively).

Icatibant tested negative for genotoxicity in the in vitro Ames bacterial reverse mutation test, in vitro Chinese hamster bone marrow chromosome aberration assay, and in vivo mouse micronucleus test.

Daily subcutaneous administration of icatibant to rats and dogs caused ovarian, uterine, and testicular atrophy/degeneration and adverse effects on the mammary and prostate glands. In rats, testicular atrophy, reduced prostate gland secretion, decreased testosterone levels and degenerate corpora lutea occurred at doses greater than or equal to 3 mg/kg (approximately 5-fold greater than the MRHD in males and 2-fold greater than the MRHD in females on an AUC basis) and a decrease in developing ovarian follicles, mammary gland masculinization, and uterine atrophy occurred at doses greater than or equal to 10 mg/kg (approximately 6-fold greater than MRHD in females on an AUC basis). In dogs, reduced sperm counts and uterine atrophy occurred at doses greater than or equal to 1 mg/kg (approximately 2-fold greater than the MRHD on an AUC basis). Atrophy of the testes and prostate with decreased testosterone levels, decreased ovary size and decreased number of developing follicles occurred at a dose of 10 mg/kg (approximately 30-fold greater than the MRHD in males and 15-fold greater than at the MRHD in females on an AUC basis).

In contrast to the effects of daily icatibant administration, toxicity to the ovary, uterus, testis, mammary gland, and prostate did not occur in dogs treated twice a week for 9 months. AUC exposures from a dose of 3 mg/kg in these dogs were 5- and 3-fold the MRHD exposures in men and women, respectively. Sperm counts and testosterone remained unaffected over the course of the study in male dogs dosed twice a week.

Reproduction studies in male mice and rats with daily administration of icatibant found no effects on fertility or reproductive performance with intravenous doses up to 81 mg/kg (approximately 5-fold greater than the MRHD on a mg/m^2 basis) or subcutaneous doses up to 10 mg/kg (approximately 11-fold greater than the MRHD on an AUC basis), respectively.

13.2 Animal Toxicology and/or Pharmacology

The B2 receptor has been implicated in the cardioprotective effects of bradykinin and antagonism of this receptor could potentially have negative cardiovascular effects during reperfusion after acute ischemia. Icatibant decreased coronary blood flow in the isolated guinea pig heart and aggravated the duration of post-ischemic reperfusion arrhythmias in the isolated rat heart. Intracoronary infusion of icatibant in an anesthetized myocardial infarction dog model increased mortality rate 2-fold over saline ischemia. There is limited human experience in acute ischemia. FIRAZYR should be used during acute coronary ischemia, unstable angina pectoris, or in the weeks following a stroke only if the benefit exceeds the theoretical risk to the patient.

14 CLINICAL STUDIES

The efficacy and safety of FIRAZYR for the treatment of acute attacks of HAE in adults were studied in three controlled clinical trials. Among the 223 patients in these studies, the mean age was 38 years, 64% were female, and 95% were white. Approximately 57% of patients reported use of attenuated androgens, antifibrinolytic agents, or C1 inhibitors. Response to therapy was primarily assessed using visual analog scores on a 100 mm scale and patient- and physician-reported symptom scores for abdominal and cutaneous pain and swelling.

Trial 1 was a randomized, placebo-controlled, double-blind, parallel-group study of 98 adult patients with a median age of 36 years. Patients who had developed moderate to severe cutaneous or abdominal or mild to moderate laryngeal attacks of HAE were randomized to receive either FIRAZYR 30 mg or placebo by subcutaneous injection. Patients with severe laryngeal attacks of HAE received open-label FIRAZYR 30 mg. The primary endpoint was assessed using a 3-item composite visual analog score (VAS), comprised of averaged assessments of skin swelling, skin pain, and abdominal pain. Response was defined as at least a 50% reduction from the pretreatment composite 3-item VAS score (Figure 2). The median time to 50% reduction in symptoms for patients with cutaneous or abdominal attacks treated with FIRAZYR (n=43) compared to placebo (n=45) was 2.0 hours [95% CI 1.5, 3.0] versus 19.8 hours [95% CI 6.1, 26.3], respectively (p<0.001).

Figure 2 Time to 50% reduction from baseline in 3-item VAS score.

Other evaluated endpoints included time to almost complete symptom relief (VAS<10 mm) and rescue medication use. In Trial 1, the median times to almost complete symptom relief were 8.0 versus 36.0 hours for FIRAZYR and placebo, respectively. In terms of rescue medication use, 3/43 (7%) patients treated with FIRAZYR used additional rescue medication in comparison to 18/45 (40%) patients treated with placebo.

In a second placebo-controlled trial and an active-controlled trial, a total of 26 and 35 patients, respectively, received FIRAZYR 30 mg for the treatment of an acute HAE attack. Across the three trials, FIRAZYR had a median time to 50% reduction from baseline symptoms ranging from 2.0 to 2.3 hours.

Recurrent attacks

In all three controlled trials, patients were eligible for treatment of subsequent attacks in an open-label extension. Patients were treated with FIRAZYR 30 mg and could receive up to 3 doses of FIRAZYR 30 mg administered at least 6 hours apart for each attack. A total of 225 patients were treated with 1,076 doses of 30 mg FIRAZYR for 987 attacks of acute HAE in these trials. In an assessment of the first 5 FIRAZYR-treated attacks (621 doses for 582 attacks), the median times to a 50% reduction from the pretreatment composite 3-itemVAS score were similar across attacks (2.0, 2.0, 2.4, 2.0, 1.5 hours). The majority (93%) of these attacks of HAE were treated with a single dose of FIRAZYR.

Laryngeal attacks

A total of 60 patients with laryngeal attacks were treated with FIRAZYR in the controlled trials. Efficacy results were similar to those observed for non-laryngeal (cutaneous and abdominal) sites of attack.

Self-administration

Self-administration of FIRAZYR by 56 patients was assessed in an open label trial. Patients who administered FIRAZYR during an acute attack of HAE had a median time to 50% reduction from the pretreatment composite 3-itemVAS score of 2.6 hours.

16 HOW SUPPLIED/STORAGE AND HANDLING

16.1 How Supplied

FIRAZYR is supplied as a single-dose, prefilled syringe for subcutaneous administration. Each syringe delivers 3 mL of a sterile solution of icatibant 30 mg (as icatibant acetate). Each glass syringe has a bromobutyl plunger stopper, which is not made of latex natural rubber.

FIRAZYR is available in cartons containing one single-dose, prefilled syringe and one 25 G Luer lock needle. NDC 54092-702-02.

FIRAZYR is also available in a pack containing 3 cartons; each carton contains one single-dose, prefilled syringe and one 25 G Luer lock needle. NDC 54092-702-03.

16.2 Storage and Handling

Keep out of the reach of children.

Store between 2 - 25° C (36 - 77° F).

Do not freeze.

Store in carton until time of administration.

17 PATIENT COUNSELING INFORMATION

Advise the patient to read the FDA-approved patient labeling (Patient Information and Instructions for Use).

17.1 Information for Patients

Patients may self-administer FIRAZYR upon recognition of an HAE attack after training under the guidance of a healthcare professional.

Patients with laryngeal symptoms should seek medical attention immediately in an appropriate healthcare facility after administration of FIRAZYR [see Warnings and Precautions (5.1)].

Injection site reactions are reported in most patients after administration of FIRAZYR. Other adverse reactions reported after administration of FIRAZYR include pyrexia, increase in transaminases, dizziness, and rash [see Adverse Reactions (6.1)].

Tiredness, drowsiness, and dizziness have been reported following the use of FIRAZYR. Patients should be advised not to drive or use machinery if they feel tired or dizzy.

Distributed by:
Takeda Pharmaceuticals America, Inc.
Cambridge, MA 02142

FIRAZYR and the FIRAZYR Logo are registered trademarks of Shire Orphan Therapies GmbH.

Takeda and are registered trademarks of Takeda Pharmaceutical Company Limited.

©2025 Takeda Pharmaceutical Company Limited. All rights reserved.

PATIENT INFORMATION
FIRAZYR® (FIR-a-zeer)
(icatibant) Injection, for subcutaneous use

Please read this Patient Information before you use FIRAZYR and each time you get a refill. There may be new information. This information does not take the place of talking with your healthcare provider about your medical condition or your treatment.

What is FIRAZYR?

- FIRAZYR is a medicine used to treat acute attacks of hereditary angioedema (HAE) in adults 18 years and older.
- It is not known if FIRAZYR is safe or effective for children under 18 years of age.

What should I tell my healthcare provider before using FIRAZYR?

Before you use FIRAZYR, tell your healthcare provider about all your medical conditions including if you:

- are pregnant or plan to become pregnant. It is not known if FIRAZYR will harm your unborn baby. You and your healthcare provider will decide if FIRAZYR is right for you.
- are breastfeeding or plan to breastfeed. It is not known if FIRAZYR passes into your breast milk. Talk to your healthcare provider about the best way to feed your baby if you use FIRAZYR.

Tell your healthcare provider about all the medicines you take, including prescription and over the counter medicines, vitamins, and herbal supplements.

How should I use FIRAZYR?

- Read the Instructions for Use at the end of this Patient Information leaflet for detailed instructions about the right way to use FIRAZYR.
- Use FIRAZYR exactly as your healthcare provider tells you to use it.
- Your healthcare provider will prescribe the right dose of FIRAZYR for you and tell you when to use it.
- Your healthcare provider will teach you or a caregiver how to give FIRAZYR injections.
- If your symptoms continue or come back, you may repeat your FIRAZYR injection at least six hours apart.
- Do not use more than 3 doses in 24 hours.
- If you have a laryngeal attack, inject FIRAZYR and then go to the nearest hospital emergency room right away.

What should I avoid while using FIRAZYR?

Tiredness, drowsiness, and dizziness can happen in people who take FIRAZYR. If this happens, do not drive a car, use machinery, or do anything that needs you to be alert.

What are the possible side effects of FIRAZYR?

The most common side effects of FIRAZYR include:

- redness, bruising, swelling, warmth, burning, itching, irritation, hives, numbness, pressure, or pain at the injection site
- fever
- too much of an enzyme called transaminase in your blood
- dizziness
- nausea
- headache
- rash

Tell your healthcare provider if you have any side effect that bothers you or that does not go away.

These are not all of the possible side effects of FIRAZYR. For more information, ask your healthcare provider or pharmacist.

Call your doctor for medical advice about side effects. You may report side effects to FDA at 1-800-FDA-1088.

How should I store FIRAZYR?

- Store FIRAZYR between 36°F to 77°F (2°C to 25°C).
- Do not freeze.
- Store FIRAZYR in the original carton until you are ready to use it.

Keep FIRAZYR and all medicines out of the reach of children.

General information about the safe and effective use of FIRAZYR

Medicines are sometimes prescribed for purposes other than those listed in a Patient Information leaflet. Do not use FIRAZYR for a condition for which it was not prescribed. Do not give FIRAZYR to other people, even if they have the same symptoms that you have. It may harm them.

This Patient Information leaflet summarizes the most important information about FIRAZYR. If you would like more information, talk with your healthcare provider. You can ask your pharmacist or healthcare provider for information about FIRAZYR that is written for health professionals.

For more information, go to www.FIRAZYR.com or call 1-877-TAKEDA-7 (1-877-825-3327).

What are the ingredients in FIRAZYR?

Active ingredient: icatibant acetate

Inactive Ingredients: sodium chloride (isotonicity reagent), glacial acetic acid (pH adjuster), sodium hydroxide (pH adjuster), and water

INSTRUCTIONS FOR USE
FIRAZYR® (FIR-a-zeer)
(icatibant)
Injection, for subcutaneous use

Step 1. Preparing your dose of FIRAZYR

- Wash your hands with soap and water.
- You will need the following supplies:
  - Your FIRAZYR carton that includes 1 single-dose FIRAZYR prefilled syringe and 1 needle.
  - 1 alcohol wipe
  - The medicine inside your FIRAZYR prefilled syringe should be clear and colorless. Do not use your FIRAZYR prefilled syringe if the solution contains particles, is cloudy, or has an unusual color.
  Figure A

Step 2. Remove the prefilled syringe and needle from the carton. See Figure B.

Figure B

Step 3. Twist the needle cap lid to break the seal (the needle should remain inside the protective needle cap until ready to use). See Figure C.

Figure C

Step 4. Remove the protective cap from the end of the pre-filled syringe by unscrewing the cap. Hold the syringe firmly. Carefully attach the needle to the prefilled syringe containing the colorless FIRAZYR solution. See Figure D.

Figure D

Step 5. Firmly screw the needle on the prefilled syringe. Be careful not to remove the needle from the needle cap. See Figure E.

Figure E

Preparing the Injection Site

Step 6. Choose the injection site. The injection site should be a fold of skin on your stomach, about 2 to 4 inches (5 to 10 cm) below your belly button on either side. See Figure F.

The area you choose for injection should be at least 2 inches (5 cm) away from any scars. Do not choose an area that is bruised, swollen, or painful.

Figure F

Step 7. Clean your FIRAZYR injection site with an alcohol wipe and allow it to dry. See Figure G.

Figure G

Injecting your FIRAZYR

Step 8. Remove the needle from the needle cap by holding the needle cap and carefully pulling the syringe. Do not pull up on the plunger. See Figure H.

Figure H

Step 9. Hold the FIRAZYR prefilled syringe in 1 hand, between your fingers and thumb. See Figure I.

Figure I

Step 10. Use your other hand to gently pinch the fold of skin you cleaned with the alcohol wipe between your thumb and fingers for your injection. See Figure J.

Figure J

Step 11. Hold the syringe between a 45-to-90 degree angle to your skin with the needle facing the fold of skin you are holding. See Figure K.

Figure K

Step 12. Hold the fold of skin. Bring the syringe to the skin and quickly insert the needle into the skin fold. See Figure L.

Figure L

Step 13. Push the plunger, at the top of the syringe, for at least 30 seconds until no FIRAZYR is in the syringe. See Figure M.

Figure M

Step 14. Release the skin fold and gently pull the needle out. See Figure N.

Figure N

Disposal of your used FIRAZYR prefilled syringe

Step 15. Place your used FIRAZYR syringe, with the needle attached, in an FDA-cleared sharps disposal container right away after use. Do not throw away (dispose of) loose needles and syringes in your household trash.

If you do not have an FDA-cleared sharps disposal container, you may use a household container that is:

- made of a heavy-duty plastic,
- can be closed with a tight-fitting, puncture-resistant lid, without sharps being able to come out,
- upright and stable during use,
- leak-resistant, and
- properly labeled to warn of hazardous waste inside the container.

When your sharps disposal container is almost full, you will need to follow your community guidelines for the right way to dispose of your sharps disposal container. There may be state or local laws about how you should throw away used needles and syringes. For more information about safe sharps disposal, and for specific information about sharps disposal in the state that you live in, go to the FDA’s website at: http://www.fda.gov/safesharpsdisposal.

Do not dispose of your sharps disposal container in your household trash unless your community guidelines permit this. Do not recycle your used sharps disposal container.

Figure O

Distributed by:
Takeda Pharmaceuticals America, Inc.
Cambridge, MA 02142

FIRAZYR and the FIRAZYR Logo are registered trademarks of Shire Orphan Therapies GmbH. Takeda and are registered trademarks of Takeda Pharmaceutical Company Limited.

©2025 Takeda Pharmaceutical Company Limited. All rights reserved.

This Patient Information and Instructions for Use have been approved by the U.S. Food and Drug Administration.

Revised: June 2025

PRINCIPAL DISPLAY PANEL - 3 mL Syringe Carton - 54092-702-03

Takeda

Prefilled Syringe

Rx ONLY
NDC 54092-702-03

Carton contains:
One single-dose,
prefilled syringe and one 25G
hypodermic needle.
Full prescribing information with
patient injection instructions.
The syringe is closed with a protective cap.

firazyr®
(icatibant injection)
30 mg/3 mL
(10 mg/mL)
FOR SUBCUTANEOUS USE ONLY

PRINCIPAL DISPLAY PANEL - 3 mL Syringe Carton - 54092-702-02

Takeda

Prefilled Syringe

Rx ONLY
NDC 54092-702-02

Carton contains:
One single-dose,
prefilled syringe and one 25G
hypodermic needle.
Full prescribing information with
patient injection instructions.
The syringe is closed with a protective cap.

firazyr®
(icatibant injection)
30 mg/3 mL
(10 mg/mL)
FOR SUBCUTANEOUS USE ONLY

PRINCIPAL DISPLAY PANEL - 3 mL Syringe Carton - 54092-702-03

Takeda

Prefilled Syringe

Rx ONLY
NDC 54092-702-03

Carton contains:
Three cartons, each with one single-dose, prefilled syringe
and one 25G hypodermic needle.
Full prescribing information with patient injection instructions.
The syringe is closed with a protective cap.

firazyr®
(icatibant injection)
30 mg/3 mL
(10 mg/mL)
FOR SUBCUTANEOUS USE ONLY